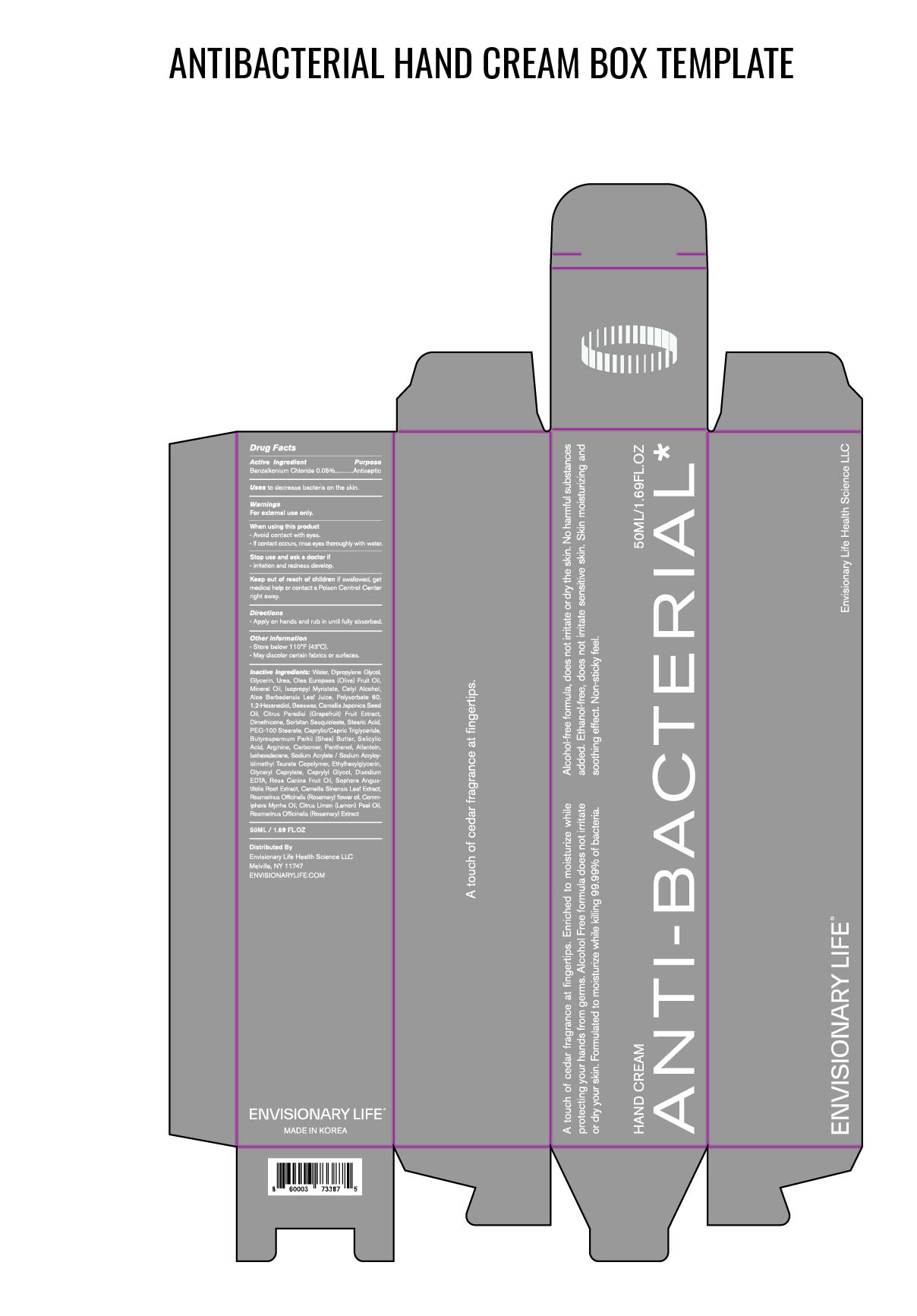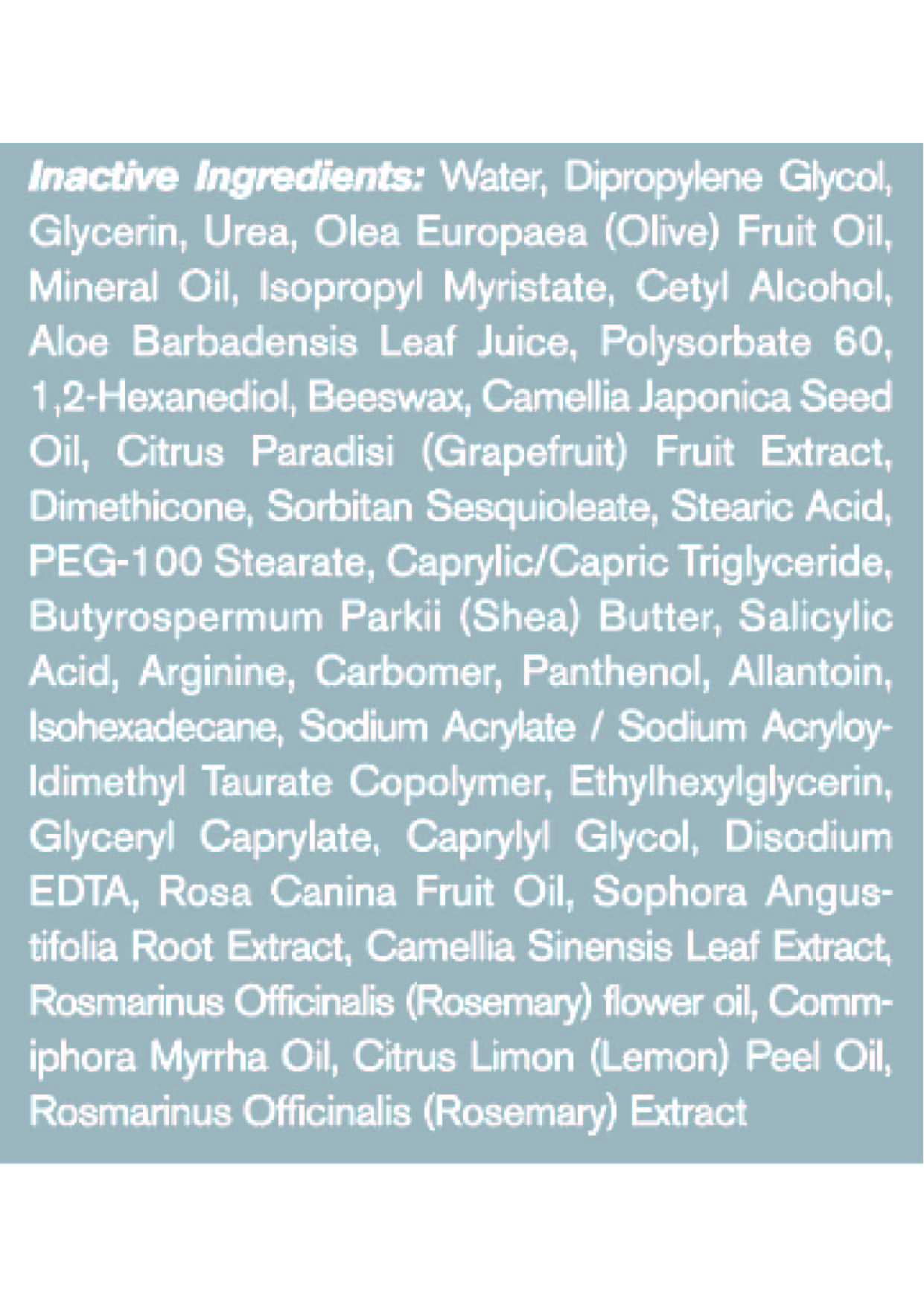 DRUG LABEL: HANDCREAM ANTI-BACTERIAL
NDC: 82416-0050 | Form: CREAM
Manufacturer: Envisionary Life Health Science LLC
Category: otc | Type: HUMAN OTC DRUG LABEL
Date: 20211124

ACTIVE INGREDIENTS: BENZALKONIUM CHLORIDE 0.025 g/50 mL
INACTIVE INGREDIENTS: YELLOW WAX; ROSEMARY; DIMETHICONE; STEARIC ACID; CARBOMER HOMOPOLYMER, UNSPECIFIED TYPE; PANTHENOL; GRAPEFRUIT; SORBITAN SESQUIOLEATE; UREA; ROSA CANINA FRUIT OIL; SOPHORA FLAVESCENS ROOT; CAPRYLYL GLYCOL; ISOPROPYL MYRISTATE; POLYSORBATE 60; 1,2-HEXANEDIOL; CAMELLIA JAPONICA SEED OIL; PEG-100 STEARATE; MEDIUM-CHAIN TRIGLYCERIDES; SALICYLIC ACID; ARGININE; EDETATE DISODIUM; OLIVE OIL; GLYCERIN; ALOE VERA LEAF; DIPROPYLENE GLYCOL; SODIUM ACRYLATE/SODIUM ACRYLOYLDIMETHYLTAURATE COPOLYMER (4000000 MW); ETHYLHEXYLGLYCERIN; GLYCERYL CAPRYLATE; ROSMARINUS OFFICINALIS FLOWER; WATER; SHEA BUTTER; ALLANTOIN; CETYL ALCOHOL; MYRRH OIL; LEMON OIL; MINERAL OIL; GREEN TEA LEAF; ISOHEXADECANE

82416-0050-02 ENVISIONARY LIFE HEALTH SCIENCE LLC
HAND CREAM ANTI-BACTERIAL

Active ingredient

Benzalkonium Chloride 0.05%

Purpose

Antiseptic

Warnings

For external use only.

Keep out of reach of children

if swallowed, get medical help or contact a Poison Control Center right away.

When using this product

- Avoid contact with eyes.
- If contact occurs, rinse eyes throughly with water.

Uses

to decrease bacteria on the skin.

Stop use and ask a doctor if

- irritation and redness develop.

Directions

- Apply on hands and rub in until fully absorbed.

OTHER SAFETY INFORMATION

- Store below 110 F (43 C)
- May discolor certain fabrics or surfaces.